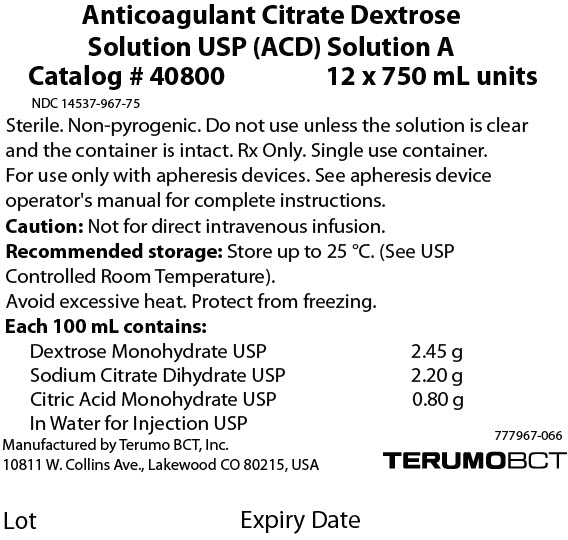 DRUG LABEL: ACD 
NDC: 14537-967 | Form: INJECTION, SOLUTION
Manufacturer: Terumo BCT Ltd
Category: prescription | Type: HUMAN PRESCRIPTION DRUG LABEL
Date: 20250122

ACTIVE INGREDIENTS: Dextrose Monohydrate 2.45 g/100 mL; SODIUM CITRATE, UNSPECIFIED FORM 2.2 g/100 mL; Citric Acid Monohydrate 0.80 g/100 mL

Anticoagulant Citrate Dextrose
Solution USP (ACD) Solution A

Catalog # 40800
12 × 750 mL units

NDC 14537-967-75

DESCRIPTION

Sterile. Non-pyrogenic. Do not use unless the solution is clear and the container is intact. Rx Only. Single use container.

For use only with apheresis devices. See apheresis device operator's manual for complete instructions.

Caution

Not for direct intravenous infusion.

Recommended storage

Store up to 25 °C. (See USP Controlled Room Temperature).

Avoid excessive heat. Protect from freezing.

HOW SUPPLIED

Each 100 mL contains:
Dextrose Monohydrate USP | 2.45 g
Sodium Citrate Dihydrate USP | 2.20 g
Citric Acid Monohydrate USP | 0.80 g
In Water for Injection USP

Manufactured by Terumo BCT, Inc.
10811 W. Collins Ave., Lakewood CO 80215, USA

777967-066

Lot
Expiry Date

PRINCIPAL DISPLAY PANEL - 12 Bag Case Label

Anticoagulant Citrate Dextrose
Solution USP (ACD) Solution A

Catalog # 40800
12 x 750 mL units

NDC 14537-967-75

Sterile. Non-pyrogenic. Do not use unless the solution is clear
and the container is intact. Rx Only. Single use container.
For use only with apheresis devices. See apheresis device
operator's manual for complete instructions.

Caution: Not for direct intravenous infusion.

Recommended storage: Store up to 25 °C. (See USP
Controlled Room Temperature).
Avoid excessive heat. Protect from freezing.

Each 100 mL contains:

Dextrose Monohydrate USP 2.45 g
Sodium Citrate Dihydrate USP 2.20 g
Citric Acid Monohydrate USP 0.80 g
In Water for Injection USP

Manufactured by Terumo BCT, Inc.
10811 W. Collins Ave., Lakewood CO 80215, USA

777967-066
TERUMOBCT

Lot
Expiry Date